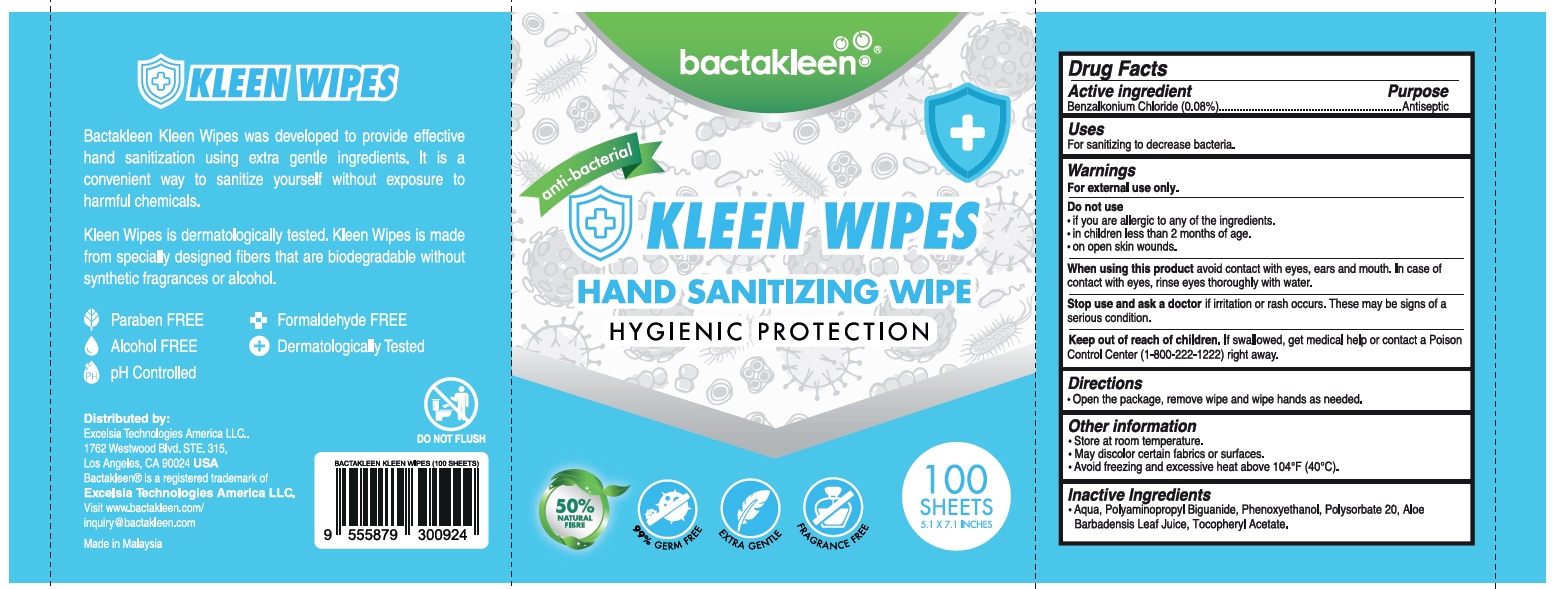 DRUG LABEL: BACTAKLEEN KLEEN WIPES
NDC: 73215-110 | Form: LIQUID
Manufacturer: Excelsia Technologies Sdn Bhd
Category: otc | Type: HUMAN OTC DRUG LABEL
Date: 20200728

ACTIVE INGREDIENTS: BENZALKONIUM CHLORIDE 0.08 g/1 1
INACTIVE INGREDIENTS: POLYSORBATE 20; .ALPHA.-TOCOPHEROL ACETATE; ALOE VERA LEAF; WATER; PHENOXYETHANOL; POLYAMINOPROPYL BIGUANIDE

BACTAKLEEN KLEEN WIPES

Active Ingredients

Benzalkonium chloride (0.08%)

Purpose

Antiseptic

Keep out of reach of children

If swallowed, get medical help or contact a Poison Control Center (1-800-222-1222) right away.

Uses

Fro sanitizing to decrease bacteria

Warnings

For external use only

Do not use if you are allergic to any of the ingredients

When using this product avoid contact with eyes. If contact occurs, rinse eyes thoroughly with water. avoid contact with broken skin

Stop use and ask a doctor if irritation or rash occurs. These may be sign of a serious condition.

DOSAGE AND ADMINISTRATION

Open the package, remove and wipe hands as needed.

Inactive Ingredients

Water. Polyaminopropyl Biguanide, Phenoxyethanol, Polysorbate 20, Aloe Barbadensis Leaf Juice, Tocopheryl Acetate.